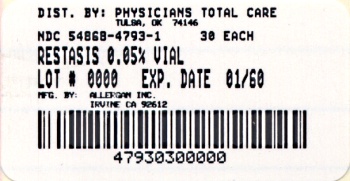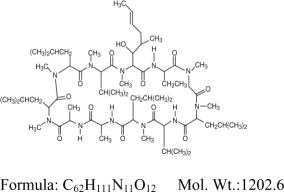 DRUG LABEL: RESTASIS
NDC: 54868-4793 | Form: EMULSION
Manufacturer: Physicians Total Care, Inc.
Category: prescription | Type: HUMAN PRESCRIPTION DRUG LABEL
Date: 20100527

ACTIVE INGREDIENTS: CYCLOSPORINE 0.5 mg/1 mL
INACTIVE INGREDIENTS: GLYCERIN; CASTOR OIL; POLYSORBATE 80; CARBOMER COPOLYMER TYPE A; WATER; SODIUM HYDROXIDE

RESTASIS®
(cyclosporine ophthalmic emulsion) 0.05%

Sterile, Preservative-Free

DESCRIPTION

RESTASIS® (cyclosporine ophthalmic emulsion) 0.05% contains a topical immunomodulator with anti-inflammatory effects. Cyclosporine's chemical name is Cyclo[[(E)-(2S,3R,4R)-3-hydroxy-4-methyl-2-(methylamino)-6-octenoyl]-L-2-aminobutyryl-N-methylglycyl-N-methyl-L-leucyl-L-valyl-N-methyl-L-leucyl-L-alanyl-D-alanyl-N-methyl-L-leucyl-N-methyl-L-leucyl-N-methyl-L-valyl] and it has the following structure:

Structural Formula

Cyclosporine is a fine white powder. RESTASIS® appears as a white opaque to slightly translucent homogeneous emulsion. It has an osmolality of 230 to 320 mOsmol/kg and a pH of 6.5-8.0. Each mL of RESTASIS® ophthalmic emulsion contains: Active: cyclosporine 0.05%. Inactives: glycerin; castor oil; polysorbate 80; carbomer copolymer type A; purified water; and sodium hydroxide to adjust pH.

CLINICAL PHARMACOLOGY

Mechanism of Action

Cyclosporine is an immunosuppressive agent when administered systemically.

In patients whose tear production is presumed to be suppressed due to ocular inflammation associated with keratoconjunctivitis sicca, cyclosporine emulsion is thought to act as a partial immunomodulator. The exact mechanism of action is not known.

Pharmacokinetics

Blood cyclosporin A concentrations were measured using a specific high pressure liquid chromatography-mass spectrometry assay. Blood concentrations of cyclosporine, in all the samples collected, after topical administration of RESTASIS® 0.05%, BID, in humans for up to 12 months, were below the quantitation limit of 0.1 ng/mL. There was no detectable drug accumulation in blood during 12 months of treatment with RESTASIS® ophthalmic emulsion.

Clinical Evaluations

Four multicenter, randomized, adequate and well-controlled clinical studies were performed in approximately 1200 patients with moderate to severe keratoconjunctivitis sicca. RESTASIS® demonstrated statistically significant increases in Schirmer wetting of 10 mm versus vehicle at six months in patients whose tear production was presumed to be suppressed due to ocular inflammation. This effect was seen in approximately 15% of RESTASIS® ophthalmic emulsion treated patients versus approximately 5% of vehicle treated patients. Increased tear production was not seen in patients currently taking topical anti-inflammatory drugs or using punctal plugs.

No increase in bacterial or fungal ocular infections was reported following administration of RESTASIS®.

INDICATIONS AND USAGE

RESTASIS® ophthalmic emulsion is indicated to increase tear production in patients whose tear production is presumed to be suppressed due to ocular inflammation associated with keratoconjunctivitis sicca. Increased tear production was not seen in patients currently taking topical anti-inflammatory drugs or using punctal plugs.

CONTRAINDICATIONS

RESTASIS® is contraindicated in patients with active ocular infections and in patients with known or suspected hypersensitivity to any of the ingredients in the formulation.

WARNING

RESTASIS® ophthalmic emulsion has not been studied in patients with a history of herpes keratitis.

PRECAUTIONS

General: For ophthalmic use only.

Information for Patients

The emulsion from one individual single-use vial is to be used immediately after opening for administration to one or both eyes, and the remaining contents should be discarded immediately after administration.

Do not allow the tip of the vial to touch the eye or any surface, as this may contaminate the emulsion.

RESTASIS® should not be administered while wearing contact lenses. Patients with decreased tear production typically should not wear contact lenses. If contact lenses are worn, they should be removed prior to the administration of the emulsion. Lenses may be reinserted 15 minutes following administration of RESTASIS® ophthalmic emulsion.

Carcinogenesis, Mutagenesis, and Impairment of Fertility

Systemic carcinogenicity studies were carried out in male and female mice and rats. In the 78-week oral (diet) mouse study, at doses of 1, 4, and 16 mg/kg/day, evidence of a statistically significant trend was found for lymphocytic lymphomas in females, and the incidence of hepatocellular carcinomas in mid-dose males significantly exceeded the control value.

In the 24-month oral (diet) rat study, conducted at 0.5, 2, and 8 mg/kg/day, pancreatic islet cell adenomas significantly exceeded the control rate in the low dose level. The hepatocellular carcinomas and pancreatic islet cell adenomas were not dose related. The low doses in mice and rats are approximately 1000 and 500 times greater, respectively, than the daily human dose of one drop (28 μL) of 0.05% RESTASIS® BID into each eye of a 60 kg person (0.001 mg/kg/day), assuming that the entire dose is absorbed.

Cyclosporine has not been found mutagenic/genotoxic in the Ames Test, the V79-HGPRT Test, the micronucleus test in mice and Chinese hamsters, the chromosome-aberration tests in Chinese hamster bone-marrow, the mouse dominant lethal assay, and the DNA-repair test in sperm from treated mice. A study analyzing sister chromatid exchange (SCE) induction by cyclosporine using human lymphocytes in vitro gave indication of a positive effect (i.e., induction of SCE).

No impairment in fertility was demonstrated in studies in male and female rats receiving oral doses of cyclosporine up to 15 mg/kg/day (approximately 15,000 times the human daily dose of 0.001 mg/kg/day) for 9 weeks (male) and 2 weeks (female) prior to mating.

Pregnancy-Teratogenic Effects

Pregnancy category C.

TERATOGENIC EFFECTS

Teratogenic Effects: No evidence of teratogenicity was observed in rats or rabbits receiving oral doses of cyclosporine up to 300 mg/kg/day during organogenesis. These doses in rats and rabbits are approximately 300,000 times greater than the daily human dose of one drop (28 μL) 0.05% RESTASIS® BID into each eye of a 60 kg person (0.001mg/kg/day), assuming that the entire dose is absorbed.

NONTERATOGENIC EFFECTS

Non-Teratogenic Effects: Adverse effects were seen in reproduction studies in rats and rabbits only at dose levels toxic to dams. At toxic doses (rats at 30 mg/kg/day and rabbits at 100 mg/kg/day), cyclosporine oral solution, USP, was embryo- and fetotoxic as indicated by increased pre- and postnatal mortality and reduced fetal weight together with related skeletal retardations. These doses are 30,000 and 100,000 times greater, respectively than the daily human dose of one drop (28 μL) of 0.05% RESTASIS® BID into each eye of a 60 kg person (0.001 mg/kg/day), assuming that the entire dose is absorbed. No evidence of embryofetal toxicity was observed in rats or rabbits receiving cyclosporine at oral doses up to 17 mg/kg/day or 30 mg/kg/day, respectively, during organogenesis. These doses in rats and rabbits are approximately 17,000 and 30,000 times greater, respectively, than the daily human dose.

Offspring of rats receiving a 45 mg/kg/day oral dose of cyclosporine from Day 15 of pregnancy until Day 21 postpartum, a maternally toxic level, exhibited an increase in postnatal mortality; this dose is 45,000 times greater than the daily human topical dose, 0.001 mg/kg/day, assuming that the entire dose is absorbed. No adverse events were observed at oral doses up to 15 mg/kg/day (15,000 times greater than the daily human dose).

There are no adequate and well-controlled studies of RESTASIS® in pregnant women. RESTASIS® should be administered to a pregnant woman only if clearly needed.

Nursing Mothers

Cyclosporine is known to be excreted in human milk following systemic administration but excretion in human milk after topical treatment has not been investigated. Although blood concentrations are undetectable after topical administration of RESTASIS® ophthalmic emulsion, caution should be exercised when RESTASIS® is administered to a nursing woman.

Pediatric Use

The safety and efficacy of RESTASIS® ophthalmic emulsion have not been established in pediatric patients below the age of 16.

Geriatric Use

No overall difference in safety or effectiveness has been observed between elderly and younger patients.

ADVERSE REACTIONS

The most common adverse event following the use of RESTASIS® was ocular burning (17%).

Other events reported in 1% to 5% of patients included conjunctival hyperemia, discharge, epiphora, eye pain, foreign body sensation, pruritus, stinging, and visual disturbance (most often blurring).

DOSAGE AND ADMINISTRATION

Invert the unit dose vial a few times to obtain a uniform, white, opaque emulsion before using. Instill one drop of RESTASIS® ophthalmic emulsion twice a day in each eye approximately 12 hours apart. RESTASIS® can be used concomitantly with artificial tears, allowing a 15 minute interval between products. Discard vial immediately after use.

HOW SUPPLIED

RESTASIS® ophthalmic emulsion is packaged in single use vials. Each vial contains 0.4 mL fill in a 0.9 mL LDPE vial; 30 vials are packaged in a polypropylene tray with an aluminum peelable lid. The entire contents of each tray (30 vials) must be dispensed intact. RESTASIS® is also provided in a 60 count (2 x 30) package (one month supply) that must be dispensed intact.

30 Vials 0.4 mL each - NDC 54868-4793-1

Storage: Store RESTASIS® ophthalmic emulsion at 15 - 25° C (59 - 77° F).

KEEP OUT OF THE REACH OF CHILDREN.

Rx Only

Revised: 02/2010

© 2010 Allergan, Inc.
Irvine, CA 92612, U.S.A.
® marks owned by Allergan, Inc.
U.S. Patent 5,474,979
Made in the U.S.A.

71876US14B

Relabeling of "Additional" bar code label by:
Physicians Total Care, Inc.
Tulsa, OK 74146

Label –

NDC 54868-4793-1

Restasis

(Cyclosporine Ophthalmic Emulsion) 0.05%

30 Single-Use Vials (0.4 mL each)

Each mL contains: Active: cyclosporine 0.05% Inactives: glycerin; castor oil; polysorbate 80; carbomer copolymer type A; purified water; and sodium hydroxide to adjust the pH. Usual Dosage: Twice daily approximately 12 hours apart. Invert the vial before using. Use immediately after opening and then discard.

Note: Store at 15 - 25° C (59 - 77° F). Store vials in the thermoformed tray until use. The entire contents of each package (60 vials) must be dispensed intact.

Rx only